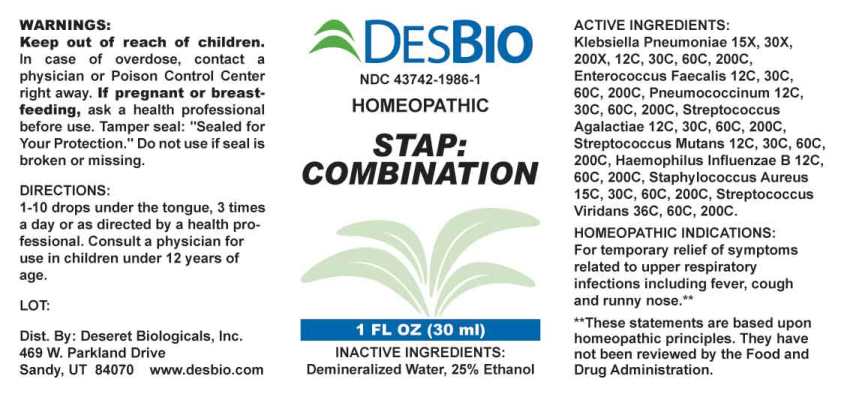 DRUG LABEL: Stap Combination
NDC: 43742-1986 | Form: LIQUID
Manufacturer: Deseret Biologicals, Inc.
Category: homeopathic | Type: HUMAN OTC DRUG LABEL
Date: 20240305

ACTIVE INGREDIENTS: KLEBSIELLA PNEUMONIAE 15 [hp_X]/1 mL; ENTEROCOCCUS FAECALIS 12 [hp_C]/1 mL; STREPTOCOCCUS PNEUMONIAE 12 [hp_C]/1 mL; STREPTOCOCCUS AGALACTIAE 12 [hp_C]/1 mL; STREPTOCOCCUS MUTANS 12 [hp_C]/1 mL; HAEMOPHILUS INFLUENZAE TYPE B 12 [hp_C]/1 mL; STAPHYLOCOCCUS AUREUS 15 [hp_C]/1 mL; STREPTOCOCCUS VIRIDANS GROUP 36 [hp_C]/1 mL
INACTIVE INGREDIENTS: WATER; ALCOHOL

DRUG FACTS:

ACTIVE INGREDIENTS:

Klebsiella Pneumoniae 15X, 30X, 200X, 12C, 30C, 60C, 200C, Enterococcus Faecalis 12C, 30C, 60C, 200C, Pneumococcinum 12C, 30C, 60C, 200C, Streptococcus Agalactiae 12C, 30C, 60C, 200C, Streptococcus Mutans 12C, 30C, 60C, 200C, Haemophilus Influenzae B 12C, 60C, 200C, Staphylococcus Aureus 15C, 30C, 60C, 200C, Streptococcus Viridans 36C, 60C, 200C.

HOMEOPATHIC INDICATIONS:

For temporary relief of symptoms related to upper respiratory infections including fever, cough and runny nose.**

**These statements are based upon homeopathic principles. They have not been reviewed by the Food and Drug Administration.

WARNINGS:

Keep out of reach of children. In case of overdose, contact a physician or Poison Control Center right away.

If pregnant or breast-feeding, ask a health professional before use.

Tamper seal: "Sealed for Your Protection." Do not use if seal is broken or missing.

Keep out of reach of children. In case of overdose, contact a physician or Poison Control Center right away.

DIRECTIONS:

1-10 drops under the tongue, 3 times a day or as directed by a health professional. Consult a physician for use in children under 12 years of age.

HOMEOPATHIC INDICATIONS:

For temporary relief of symptoms related to upper respiratory infections including fever, cough and runny nose.**

**These statements are based upon homeopathic principles. They have not been reviewed by the Food and Drug Administration.

INACTIVE INGREDIENTS:

Demineralized Water, 25% Ethanol

QUESTIONS:

Dist. By: Deseret Biologicals, Inc.
469 W. Parkland Drive
Sandy, UT 84070 www.desbio.com

PACKAGE LABEL DISPLAY:

DESBIO

NDC 43742-1986-1

HOMEOPATHIC

STAP: COMBINATION

1 FL OZ (30 ml)